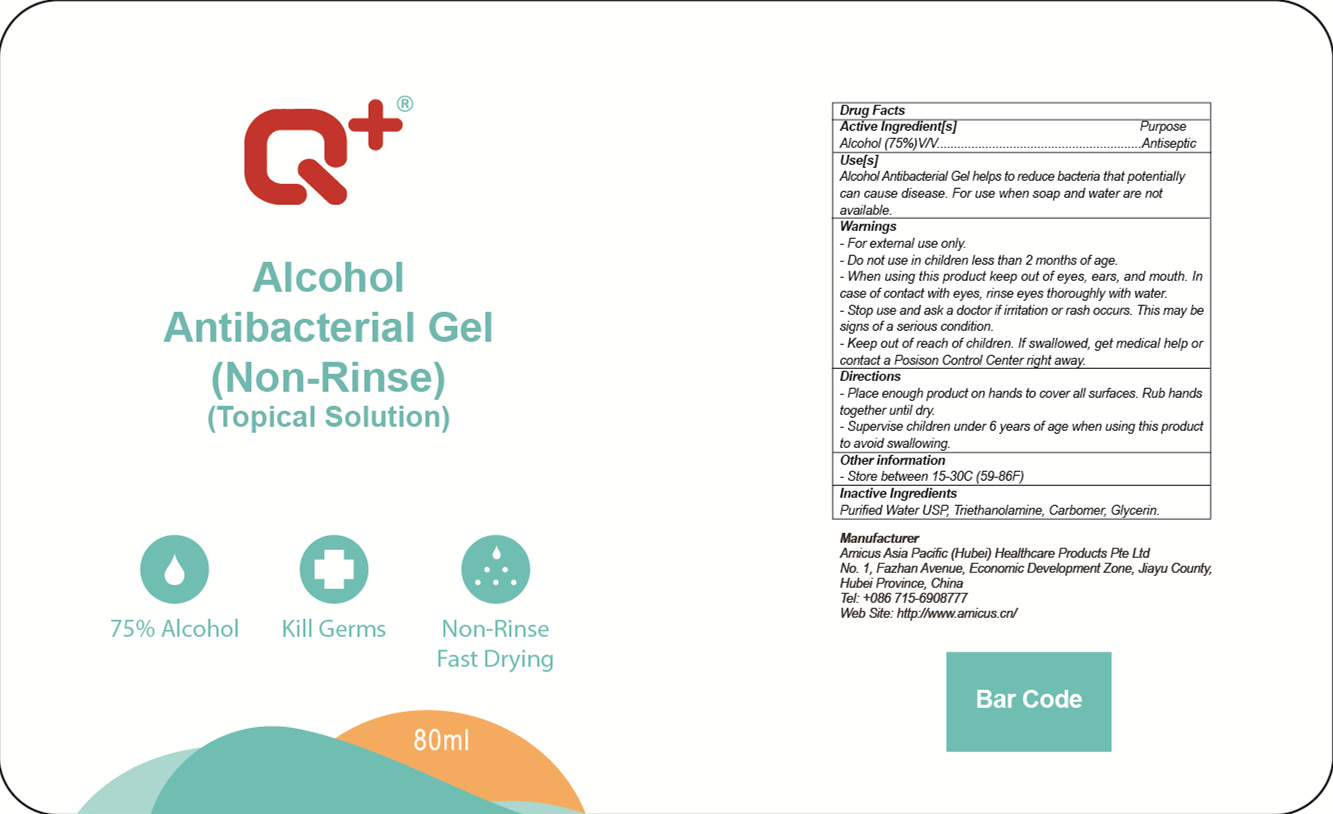 DRUG LABEL: Alcohol Antibacterial Gel(None-Rinse)
NDC: 54345-002 | Form: GEL
Manufacturer: Amicus Asia Pacific(Hubei) Healthcare Products Pte Ltd
Category: otc | Type: HUMAN OTC DRUG LABEL
Date: 20200703

ACTIVE INGREDIENTS: ALCOHOL 60 mL/80 mL
INACTIVE INGREDIENTS: WATER; TROLAMINE; CARBOMER HOMOPOLYMER, UNSPECIFIED TYPE; GLYCERIN

DOSAGE AND ADMINISTRATION

Store between 15- 30°C (59-86°F)

INACTIVE INGREDIENT

Purified Water USP, Triethanolamine，Carbomer，Glycerin

INDICATIONS AND USAGE

Place enough product on hands to cover all surfaces. Rub hands together until dry.

ACTIVE INGREDIENT

Alcohol

keep out of reach of children

PURPOSE

Disinfection
Sterilization
No Rinseing

WARNINGS

1.For extermal use only.
2.Do not use in children less than 2 months of age.
3.When using this product keep out of eyes, ears, and mouth. In case of contact with eyes, rinse eyes thoroughly with water.
4.Stop use and ask a doctor if iritation or rash occurs. This may be signs of a serious condition.
5.Keep out of reach of children. If swallowed, get medical help or contact a Posison Control Center right away.